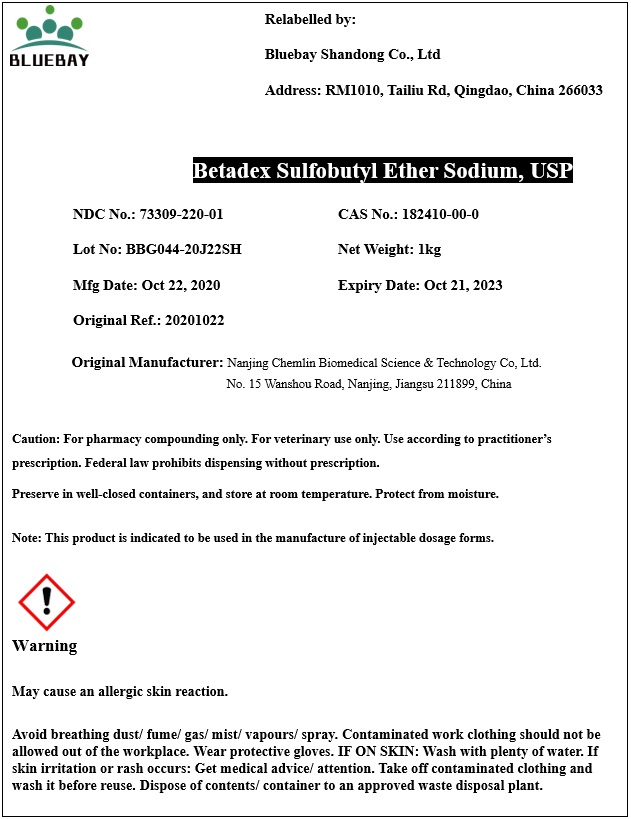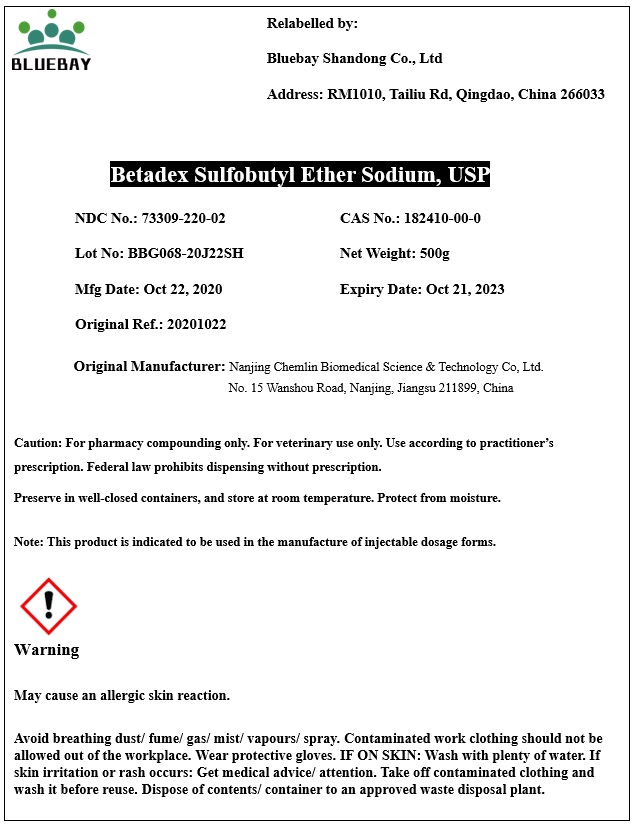 DRUG LABEL: Betadex Sulfobutyl Ether Sodium
NDC: 73309-220 | Form: POWDER
Manufacturer: BLUEBAY SHANDONG CO.,LTD
Category: other | Type: BULK INGREDIENT
Date: 20210127

ACTIVE INGREDIENTS: BETADEX SULFOBUTYL ETHER SODIUM 1 kg/1 kg

Betadex Sulfobutyl Ether Sodium